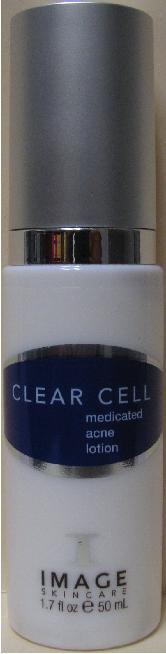 DRUG LABEL: CLEAR CELL Medicated Acne
NDC: 62742-4035 | Form: LOTION
Manufacturer: Allure Labs, Inc.
Category: otc | Type: HUMAN OTC DRUG LABEL
Date: 20100701

ACTIVE INGREDIENTS: BENZOYL PEROXIDE 50 mg/1 mL; SALICYLIC ACID 30 mg/1 mL

DRUG FACTS

Active Ingredients:

Benzoyl Peroxide 5.00%

Salicylic Acid 3.00%

Inactive Ingredients:

Aqua (Water), Aloe barbadensis leaf extract, Caprylic/Capric Triglyceride, Cetearyl Olivate, Sorbitan Olivate, PEG-7 Glyceryl Cocoate, Extracts of Malva sylvestris (Mallow), Mentha piperita (Peppermint) leaf, Primula veris, Alchemilla vulgaris, Veronica officinalis, Melissa officinalis leaf, Achillea millefolium, Tocopheryl acetate (Vitamin E), Camellia sinensis leaf extract, Arnica montana flower extract, Chamomilla recutita flower extract, Aesculus hippocastanum (Horse Chestnut) extract, Melia azadirachta leaf extract, Melaleuca alternifolia leaf oil, Mentha virdis (Spearmint) oil, Eucalyptus globulus leaf oil, Disodium EDTA.

PACKAGE LABEL

Information on the back of the container:

(Claims)

A daily oil-free lotion to control over production of oil and bacteria. An anti-oxidant blend improves hydration and health of acne skin. Natural skin lighteners diminish redness of acne lesions.

Paraben-free

DIRECTIONS:

Apply to cleasnsed skin every morning and evening. May be used as spot treatment daily to diminish acne lesions.

INDICATIONS:

Acne and acne prone skin.

DISTRIBUTOR:

Image International

Palm Beach, FL 33411 USA

www.imageskincare.com

Image of the product:

CLEAR CELL Medicated Acne Lotion